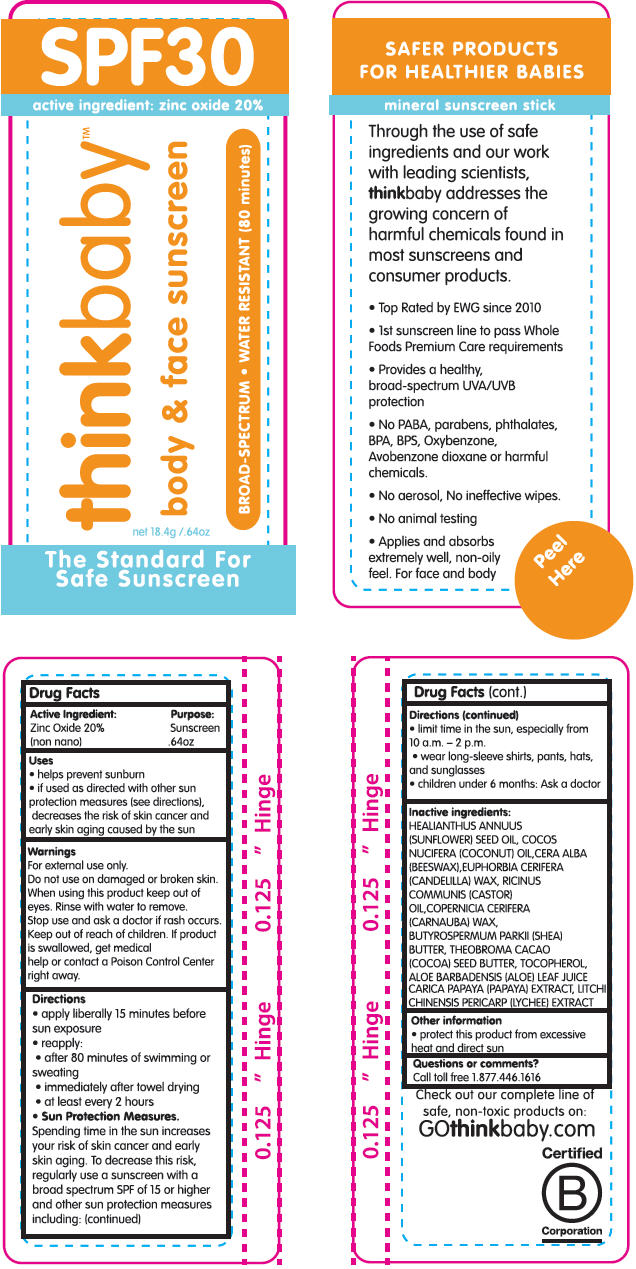 DRUG LABEL: Thinkbaby
NDC: 60781-2003 | Form: STICK
Manufacturer: thinkOperations,LLC
Category: otc | Type: HUMAN OTC DRUG LABEL
Date: 20190325

ACTIVE INGREDIENTS: ZINC OXIDE 200 mg/1 g
INACTIVE INGREDIENTS: SUNFLOWER OIL; COCONUT OIL; WHITE WAX; CANDELILLA WAX; CASTOR OIL; CARNAUBA WAX; SHEA BUTTER; COCOA BUTTER; TOCOPHEROL; ALOE VERA LEAF

Thinkbaby™ Sunscreen SPF 30

Drug Facts

Active Ingredient

Zinc Oxide 20%
(non nano)

Purpose

Sunscreen
.64oz

Uses

- helps prevent sunburn
- if used as directed with other sun protection measures (see directions), decreases the risk of skin cancer and early skin aging caused by the sun

Warnings

For external use only.

Do not use on damaged or broken skin.

When using this product keep out of eyes. Rinse with water to remove.

Stop use and ask a doctor if rash occurs.

Keep out of reach of children. If product is swallowed, get medical help or contact a Poison Control Center right away.

Directions

- apply liberally 15 minutes before sun exposure
- reapply:
  - after 80 minutes of swimming or sweating
  - immediately after towel drying
  - at least every 2 hours
- Sun Protection Measures. Spending time in the sun increases your risk of skin cancer and early skin aging. To decrease this risk, regularly use a sunscreen with a broad spectrum SPF of 15 or higher and other sun protection measures including:
  - limit time in the sun, especially from 10 a.m. – 2 p.m.
  - wear long-sleeve shirts, pants, hats, and sunglasses
- children under 6 months: Ask a doctor

Inactive ingredients

HEALIANTHUS ANNUUS (SUNFLOWER) SEED OIL, COCOS NUCIFERA (COCONUT) OIL,CERA ALBA (BEESWAX),EUPHORBIA CERIFERA (CANDELILLA) WAX, RICINUS COMMUNIS (CASTOR) OIL,COPERNICIA CERIFERA (CARNAUBA) WAX, BUTYROSPERMUM PARKII (SHEA) BUTTER, THEOBROMA CACAO (COCOA) SEED BUTTER, TOCOPHEROL, ALOE BARBADENSIS (ALOE) LEAF JUICE CARICA PAPAYA (PAPAYA) EXTRACT, LITCHI CHINENSIS PERICARP (LYCHEE) EXTRACT

Other information

- protect this product from excessive heat and direct sun

Questions or comments?

Call toll free 1.877.446.1616

PRINCIPAL DISPLAY PANEL - 18.4 g Cylinder Label

SPF30

active ingredient: zinc oxide 20%

thinkbaby™

body & face sunscreen

BROAD-SPECTRUM • WATER RESISTANT (80 minutes)

net 18.4g /.64oz

The Standard For
Safe Sunscreen